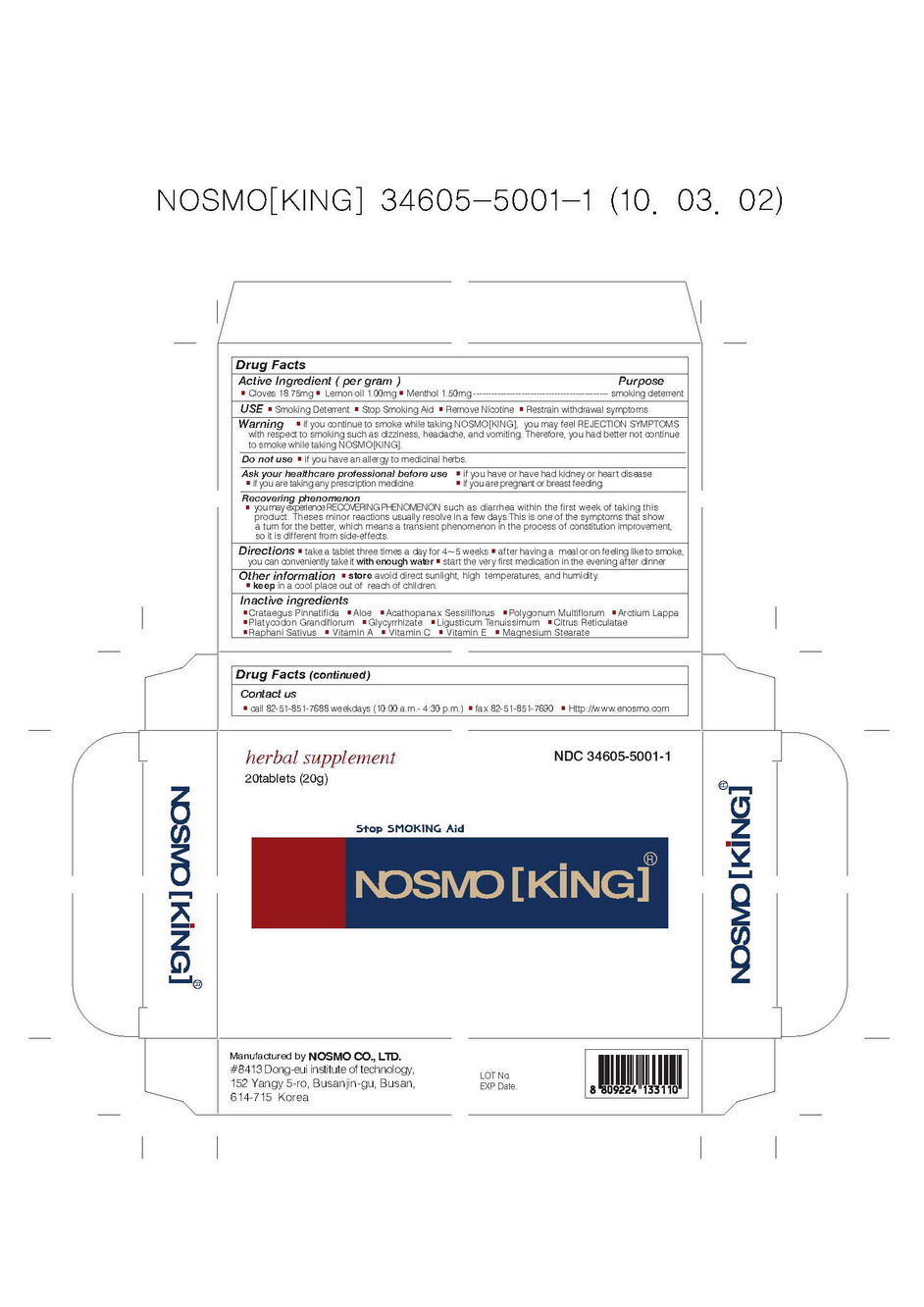 DRUG LABEL: NOSMO KING
NDC: 34605-5001 | Form: TABLET, SOLUBLE
Manufacturer: Nosmo Co., Ltd
Category: otc | Type: HUMAN OTC DRUG LABEL
Date: 20100317

ACTIVE INGREDIENTS: clove 0.11875 g/1 1; lemon 0.001 g/1 1; menthol 0.0015 g/1 1

Drug Facts

Active Ingredients: Cloves, Lemon oil, Menthol

DESCRIPTION

Nosmo king is natural herb supplement is known to help smokers
obstain from smoking by greatly reducing withdrawal symptoms
causing cravings to smoke
Effect
■ Smoking Deterrent, Stop Smoking Aid, Remove Nicotine, Restrain
withdrawal Symptoms
Warning
■ do not take if you have an allergy to medicinal herbs
■ do not take if you are pregnant or breast feeding
Directions
■ take a tablet four times a day for 4~5 weeks
■ after having a meal or on feeling like to smoke, you can conveniently
take it with enough water
■ start the very first medication in the evening after dinner
Caution
■ keep in a cool place
■ keep out of reach of children
■ avoid exposing the product direct to sunlight, high temperatures and humidity